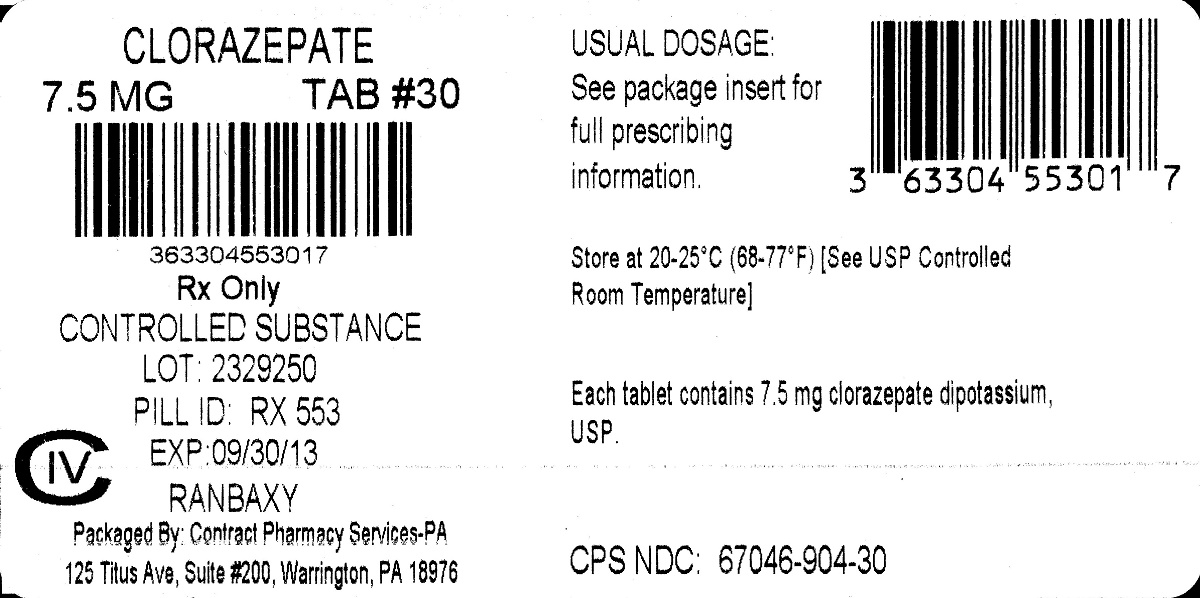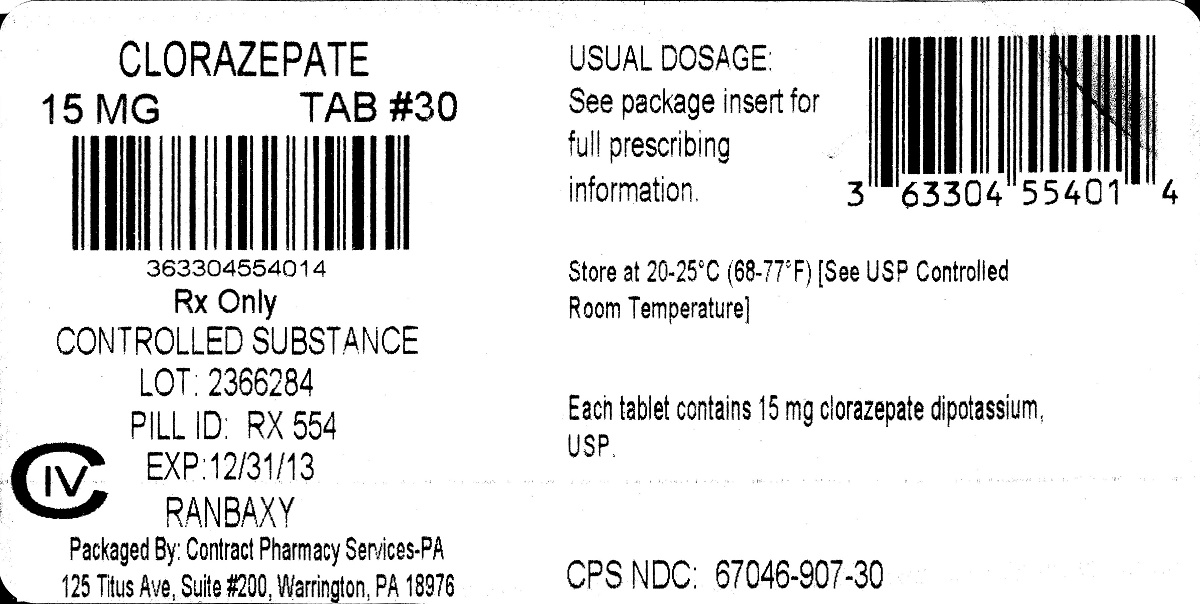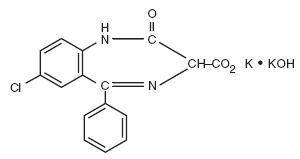 DRUG LABEL: Clorazepate dipotassium
NDC: 67046-904 | Form: TABLET
Manufacturer: Contract Pharmacy Services-PA
Category: prescription | Type: HUMAN PRESCRIPTION DRUG LABEL
Date: 20170928
DEA Schedule: CIV

ACTIVE INGREDIENTS: CLORAZEPATE DIPOTASSIUM 7.5 mg/1 1
INACTIVE INGREDIENTS: SILICON DIOXIDE; MAGNESIUM OXIDE; MAGNESIUM STEARATE; POTASSIUM CARBONATE; POTASSIUM CHLORIDE; CELLULOSE, MICROCRYSTALLINE; FD&C YELLOW NO. 6

904 Clorazepate 7.5 mg
907 Clorazepate 15 mg

Rx only

DESCRIPTION

Chemically, clorazepate dipotassium is a benzodiazepine. The molecular formula is C16H11ClK2N2O4; the molecular weight is 408.92; 1 H-1, 4-Benzodiazepine-3-carboxylic acid, 7-chloro-2,3-dihydro- 2-oxo-5-phenyl-, potassium salt compound with potassium hydroxide (1:1) and the structural formula may be represented as follows:

The compound occurs as a light yellow, crystalline powder. It darkens on exposure to light. It is soluble in water but upon standing may precipitate from the solution, slightly soluble in alcohol and in isopropyl alcohol, practically insoluble in acetone, in benzene, in chloroform, in ether and in methylene chloride.

Clorazepate dipotassium tablets, USP contain either 3.75 mg, 7.5 mg or 15 mg of clorazepate dipotassium, USP for oral administration.

Inactive ingredients for clorazepate dipotassium tablets, USP: colloidal silicon dioxide, FD&C Blue No. 2 aluminum lake (3.75 mg only), FD&C Yellow No. 6 aluminum lake (7.5 mg only), FD&C Red No. 40 aluminum lake (15 mg only), magnesium oxide, magnesium stearate, microcrystalline cellulose, potassium carbonate, and potassium chloride.

CLINICAL PHARMACOLOGY

Pharmacologically, clorazepate dipotassium has the characteristics of the benzodiazepines. It has depressant effects on the central nervous system. The primary metabolite, nordiazepam, quickly appears in the blood stream. The serum half-life is about 2 days. The drug is metabolized in the liver and excreted primarily in the urine.

Studies in healthy men have shown that clorazepate dipotassium has depressant effects on the central nervous system. Prolonged administration of single daily doses as high as 120 mg was without toxic effects. Abrupt cessation of high doses was followed in some patients by nervousness, insomnia, irritability, diarrhea, muscle aches, or memory impairment.

Since orally administered clorazepate dipotassium is rapidly decarboxylated to form nordiazepam, there is essentially no circulating parent drug. Nordiazepam, the primary metabolite, quickly appears in the blood and is eliminated from the plasma with an apparent half-life of about 40 to 50 hours. Plasma levels of nordiazepam increase proportionally with clorazepate dipotassium dose and show moderate accumulation with repeated administration. The protein binding of nordiazepam in plasma is high (97 to 98%).

Within 10 days after oral administration of a 15 mg (50µCi) dose of^14C-clorazepate dipotassium to two volunteers, 62 to 67% of the radioactivity was excreted in the urine and 15 to 19% was eliminated in the feces. Both subjects were still excreting measurable amounts of radioactivity in the urine (about 1% of the^14C-dose) on day ten.

Nordiazepam is further metabolized by hydroxylation. The major urinary metabolite is conjugated oxazepam (3-hydroxynordiazepam), and smaller amounts of conjugated p-hydroxynordiazepam and nordiazepam are also found in the urine.

INDICATIONS AND USAGE

Clorazepate dipotassium tablets, USP are indicated for the management of anxiety disorders or for the short-term relief of the symptoms of anxiety. Anxiety or tension associated with the stress of everyday life usually does not require treatment with an anxiolytic.

Clorazepate dipotassium tablets, USP are indicated as adjunctive therapy in the management of partial seizures.

The effectiveness of clorazepate dipotassium tablets, USP in long-term management of anxiety, that is, more than 4 months, has not been assessed by systematic clinical studies. Long-term studies in epileptic patients, however, have shown continued therapeutic activity. The physician should reassess periodically the usefulness of the drug for the individual patient.

Clorazepate dipotassium tablets, USP are indicated for the symptomatic relief of acute alcohol withdrawal.

CONTRAINDICATIONS

Clorazepate dipotassium tablets are contraindicated in patients with a known hypersensitivity to the drug and in those with acute narrow angle glaucoma.

WARNINGS

Use in Depressive Neuroses or Psychotic Reactions: Clorazepate dipotassium tablets are not recommended for use in depressive neuroses or in psychotic reactions.

Use in Children: Because of the lack of sufficient clinical experience, clorazepate dipotassium tablets are not recommended for use in patients less than 9 years of age.

Interference with Psychomotor Performance: Patients taking clorazepate dipotassium tablets should be cautioned against engaging in hazardous occupations requiring mental alertness, such as operating dangerous machinery including motor vehicles.

Concomitant Use with CNS Depressants: Since clorazepate dipotassium has a central nervous system depressant effect, patients should be advised against the simultaneous use of other CNS depressant drugs, and cautioned that the effects of alcohol may be increased.

Physical and Psychological Dependence: Withdrawal symptoms (similar in character to those noted with barbiturates and alcohol) have occurred following abrupt discontinuance of clorazepate. Withdrawal symptoms associated with the abrupt discontinuation of benzodiazepines have included convulsions, delirium, tremor, abdominal and muscle cramps, vomiting, sweating, nervousness, insomnia, irritability, diarrhea, and memory impairment. The more severe withdrawal symptoms have usually been limited to those patients who had received excessive doses over an extended period of time. Generally milder withdrawal symptoms have been reported following abrupt discontinuance of benzodiazepines taken continuously at therapeutic levels for several months. Consequently, after extended therapy, abrupt discontinuation of clorazepate should generally be avoided and a gradual dosage tapering schedule followed.

Caution should be observed in patients who are considered to have a psychological potential for drug dependence.

Evidence of drug dependence has been observed in dogs and rabbits which was characterized by convulsive seizures when the drug was abruptly withdrawn or the dose was reduced; the syndrome in dogs could be abolished by administration of clorazepate.

Suicidal Behavior and Ideation

Antiepileptic drugs (AEDs), including clorazepate dipotassium, increase the risk of suicidal thoughts or behavior in patients taking these drugs for any indication. Patients treated with any AED for any indication should be monitored for the emergence or worsening of depression, suicidal thoughts or behavior, and/or any unusual changes in mood or behavior.

Pooled analyses of 199 placebo-controlled clinical trials (mono- and adjunctive therapy) of 11 different AEDs showed that patients randomized to one of the AEDs had approximately twice the risk (adjusted Relative Risk 1.8, 95% CI:1.2, 2.7) of suicidal thinking or behavior compared to patients randomized to placebo. In these trials, which had a median treatment duration of 12 weeks, the estimated incidence rate of suicidal behavior or ideation among 27,863 AED-treated patients was 0.43%, compared to 0.24% among 16,029 placebo-treated patients, representing an increase of approximately one case of suicidal thinking or behavior for every 530 patients treated. There were four suicides in drug-treated patients in the trials and none in placebo-treated patients, but the number is too small to allow any conclusion about drug effect on suicide.

The increased risk of suicidal thoughts or behavior with AEDs was observed as early as one week after starting drug treatment with AEDs and persisted for the duration of treatment assessed. Because most trials included in the analysis did not extend beyond 24 weeks, the risk of suicidal thoughts or behavior beyond 24 weeks could not be assessed.

The risk of suicidal thoughts or behavior was generally consistent among drugs in the data analyzed. The finding of increased risk with AEDs of varying mechanisms of action and across a range of indications suggests that the risk applies to all AEDs used for any indication. The risk did not vary substantially by age (5 to 100 years) in the clinical trials analyzed. Table 1 shows absolute and relative risk by indication for all evaluated AEDs.

Table 1: Risk by indication for antiepileptic drugs in the pooled analysis
Indication | Placebo Patientswith Events Per 1000 Patients | Drug Patientswith Events Per 1000 Patients | Relative Risk: Incidence of Events in Drug Patients/Incidencein Placebo Patients | Risk Difference: Additional Drug Patients with Events Per 1000 Patients
Epilepsy | 1 | 3.4 | 3.5 | 2.4
Psychiatric | 5.7 | 8.5 | 1.5 | 2.9
Other | 1 | 1.8 | 1.9 | 0.9
Total | 2.4 | 4.3 | 1.8 | 1.9

The relative risk for suicidal thoughts or behavior was higher in clinical trials for epilepsy than in clinical trials for psychiatric or other conditions, but the absolute risk differences were similar for the epilepsy and psychiatric indications.

Anyone considering prescribing clorazepate dipotassium or any other AED must balance the risk of suicidal thoughts or behavior with the risk of untreated illness. Epilepsy and many other illnesses for which AEDs are prescribed are themselves associated with morbidity and mortality and an increased risk of suicidal thoughts and behavior. Should suicidal thoughts and behavior emerge during treatment, the prescriber needs to consider whether the emergence of these symptoms in any given patient may be related to the illness being treated.

Patients, their caregivers, and families should be informed that AEDs increase the risk of suicidal thoughts and behavior and should be advised of the need to be alert for the emergence or worsening of the signs and symptoms of depression, any unusual changes in mood or behavior, or the emergence of suicidal thoughts, behavior, or thoughts about self-harm. Behaviors of concern should be reported immediately to healthcare providers.

Usage in Pregnancy: An increased risk of congenital malformations associated with the use of minor tranquilizers (chlordiazepoxide, diazepam, and meprobamate) during the first trimester of pregnancy has been suggested in several studies. Clorazepate dipotassium, a benzodiazepine derivative, has not been studied adequately to determine whether it, too, may be associated with an increased risk of fetal abnormality. Because use of these drugs is rarely a matter of urgency, their use during this period should almost always be avoided. The possibility that a woman of childbearing potential may be pregnant at the time of institution of therapy should be considered. Patients should be advised that if they become pregnant during therapy or intend to become pregnant they should communicate with their physician about the desirability of discontinuing the drug.

To provide information regarding the effects of in utero exposure to clorazepate dipotassium, physicians are advised to recommend that pregnant patients taking clorazepate dipotassium enroll in the North American Antiepileptic Drug (NAAED) Pregnancy Registry. This can be done by calling the toll-free number 1-888-233-2334, and must be done by patients themselves. Information on the registry can also be found at the website http://www.aedpregnancyregistry.org/.

Usage during Lactation: Clorazepate dipotassium tablets should not be given to nursing mothers since it has been reported that nordiazepam is excreted in human breast milk.

PRECAUTIONS

In those patients in which a degree of depression accompanies the anxiety, suicidal tendencies may be present and protective measures may be required. The least amount of drug that is feasible should be available to the patient.

Patients taking clorazepate dipotassium tablets for prolonged periods should have blood counts and liver function tests periodically. The usual precautions in treating patients with impaired renal or hepatic function should also be observed.

In elderly or debilitated patients, the initial dose should be small, and increments should be made gradually, in accordance with the response of the patient, to preclude ataxia or excessive sedation.

Information for Patients:

To assure the safe and effective use of benzodiazepines, patients should be informed that, since benzodiazepines may produce psychological and physical dependence, it is essential that they consult with their physician before either increasing the dose or abruptly discontinuing this drug.

Patients, their caregivers, and families should be counseled that AEDs, including clorazepate dipotassium, may increase the risk of suicidal thoughts and behavior and should be advised of the need to be alert for the emergence or worsening of symptoms of depression, any unusual changes in mood or behavior, or the emergence of suicidal thoughts, behavior, or thoughts about self-harm. Behaviors of concern should be reported immediately to healthcare providers.

Patients should be encouraged to enroll in the NAAED Pregnancy Registry if they become pregnant. This registry is collecting information about the safety of antiepileptic drugs during pregnancy. To enroll, patients can call the toll-free number 1-888-233-2334 (see Usage in Pregnancy).

Prescribers or other health professionals should inform patients, their families, and their caregivers about the benefits and risks associated with treatment with clorazepate dipotassium and should counsel them in its appropriate use. A patient Medication Guide is available for clorazepate dipotassium. The prescriber or health professional should instruct patients, their families, and their caregivers to read the Medication Guide and should assist them in understanding its contents. Patients should be given the opportunity to discuss the contents of the Medication Guide and to obtain answers to any questions they may have. The complete text of the Medication Guide is available at www.ranbaxyusa.com.

Pediatric Use

See WARNINGS.

Geriatric Use

Clinical studies of clorazepate dipotassium were not adequate to determine whether subjects aged 65 and over respond differently than younger subjects. Elderly or debilitated patients may be especially sensitive to the effects of all benzodiazepines, including clorazepate dipotassium. In general, elderly or debilitated patients should be started on lower doses of clorazepate dipotassium and observed closely, reflecting the greater frequency of decreased hepatic, renal, or cardiac function, and of concomitant disease or other drug therapy. Dose adjustments should also be made slowly, and with more caution in this patient population (see PRECAUTIONS and DOSAGE AND ADMINISTRATION).

ADVERSE REACTIONS

The side effect most frequently reported was drowsiness. Less commonly reported (in descending order of occurrence) were: dizziness, various gastrointestinal complaints, nervousness, blurred vision, dry mouth, headache, and mental confusion. Other side effects included insomnia, transient skin rashes, fatigue, ataxia, genitourinary complaints, irritability, diplopia, depression, tremor, and slurred speech.

There have been reports of abnormal liver and kidney function tests and of decrease in hematocrit.

Decrease in systolic blood pressure has been observed.

To report SUSPECTED ADVERSE REACTIONS, contact Ranbaxy Pharmaceuticals Inc. at 1-888-Ranbaxy (726-2299) or FDA at 1-800-FDA-1088 or www.fda.gov/medwatch.

DOSAGE AND ADMINISTRATION

For the symptomatic relief of anxiety: Clorazepate dipotassium tablets are administered orally in divided doses. The usual daily dose is 30 mg. The dose should be adjusted gradually within the range of 15 to 60 mg daily in accordance with the response of the patient. In elderly or debilitated patients it is advisable to initiate treatment at a daily dose of 7.5 to 15 mg.

Clorazepate dipotassium tablets may also be administered in a single dose daily at bedtime; the recommended initial dose is 15 mg. After the initial dose, the response of the patient may require adjustment of subsequent dosage. Lower doses may be indicated in the elderly patient. Drowsiness may occur at the initiation of treatment and with dosage increment.

For the symptomatic relief of acute alcohol withdrawal:

The following dosage schedule is recommended:

1st 24 hours (Day 1) | 30 mg initially; followed by 30 to 60 mg in divided doses
2nd 24 hours (Day 2) | 45 to 90 mg in divided doses
3rd 24 hours (Day 3) | 22.5 to 45 mg in divided doses
Day 4 | 15 to 30 mg in divided doses

Thereafter, gradually reduce the daily dose to 7.5 to 15 mg. Discontinue drug therapy as soon as patient's condition is stable.

The maximum recommended total daily dose is 90 mg. Avoid excessive reductions in the total amount of drug administered on successive days.

As an Adjunct to Antiepileptic Drugs: In order to minimize drowsiness, the recommended initial dosages and dosage increments should not be exceeded.

Adults: The maximum recommended initial dose in patients over 12 years old is 7.5 mg three times a day. Dosage should be increased by no more than 7.5 mg every week and should not exceed 90 mg/day.

Children (9 to 12 years): The maximum recommended initial dose is 7.5 mg two times a day. Dosage should be increased by no more than 7.5 mg every week and should not exceed 60 mg/day.

DRUG INTERACTIONS

If clorazepate dipotassium is to be combined with other drugs acting on the central nervous system, careful consideration should be given to the pharmacology of the agents to be employed. Animal experience indicates that clorazepate dipotassium prolongs the sleeping time after hexobarbital or after ethyl alcohol, increases the inhibitory effects of chlorpromazine, but does not exhibit monoamine oxidase inhibition. Clinical studies have shown increased sedation with concurrent hypnotic medications. The actions of the benzodiazepines may be potentiated by barbiturates, narcotics, phenothiazines, monoamine oxidase inhibitors or other antidepressants.

If clorazepate dipotassium tablets are used to treat anxiety associated with somatic disease states, careful attention must be paid to possible drug interaction with concomitant medication.

In bioavailability studies with normal subjects, the concurrent administration of antacids at therapeutic levels did not significantly influence the bioavailability of clorazepate dipotassium tablets.

OVERDOSAGE

Overdosage is usually manifested by varying degrees of CNS depression ranging from slight sedation to coma. As in the management of overdosage with any drug, it should be borne in mind that multiple agents may have been taken.

The treatment of overdosage should consist of the general measures employed in the management of overdosage of any CNS depressant. Gastric evacuation either by the induction of emesis, lavage, or both, should be performed immediately. General supportive care, including frequent monitoring of the vital signs and close observation of the patient, is indicated. Hypotension, though rarely reported, may occur with large overdoses. In such cases the use of agents such as norepinephrine bitartrate injection, USP or metaraminol bitartrate injection, USP should be considered.

While reports indicate that individuals have survived overdoses of clorazepate dipotassium as high as 450 to 675 mg, these doses are not necessarily an accurate indication of the amount of drug absorbed since the time interval between ingestion and the institution of treatment was not always known. Sedation in varying degrees was the most common physiological manifestation of clorazepate dipotassium overdosage. Deep coma when it occurred was usually associated with the ingestion of other drugs in addition to clorazepate dipotassium.

Flumazenil, a specific benzodiazepine receptor antagonist, is indicated for the complete or partial reversal of the sedative effects of benzodiazepines and may be used in situations when an overdose with a benzodiazepine is known or suspected. Prior to the administration of flumazenil, necessary measures should be instituted to secure airway, ventilation, and intravenous access. Flumazenil is intended as an adjunct to, not as a substitute for, proper management of benzodiazepine overdose. Patients treated with flumazenil should be monitored for resedation, respiratory depression, and other residual benzodiazepine effects for an appropriate period after treatment. The prescriber should be aware of a risk of seizure in association with flumazenil treatment, particularly in long-term benzodiazepine users and in cyclic antidepressant overdose. The complete flumazenil package insert including CONTRAINDICATIONS, WARNINGS, and PRECAUTIONS should be consulted prior to use.

ANIMAL PHARMACOLOGY AND TOXICOLOGY

Studies in rats and monkeys have shown a substantial difference between doses producing tranquilizing, sedative and toxic effects. In rats, conditioned avoidance response was inhibited at an oral dose of 10 mg/kg; sedation was induced at 32 mg/kg; the LD50 was 1320 mg/kg. In monkeys aggressive behavior was reduced at an oral dose of 0.25 mg/kg; sedation (ataxia) was induced at 7.5 mg/kg; the LD50 could not be determined because of the emetic effect of large doses, but the LD50 exceeds 1600 mg/kg.

Twenty-four dogs were given clorazepate dipotassium orally in a 22-month toxicity study; doses up to 75 mg/kg were given. Drug-related changes occurred in the liver; weight was increased and cholestasis with minimal hepatocellular damage was found, but lobular architecture remained well preserved.

Eighteen rhesus monkeys were given oral doses of clorazepate dipotassium from 3 to 36 mg/kg daily for 52 weeks. All treated animals remained similar to control animals. Although total leucocyte count remained within normal limits it tended to fall in the female animals on the highest doses.

Examination of all organs revealed no alterations attributable to clorazepate dipotassium. There was no damage to liver function or structure.

Reproduction Studies: Standard fertility, reproduction, and teratology studies were conducted in rats and rabbits. Oral doses in rats up to 150 mg/kg and in rabbits up to 15 mg/kg produced no abnormalities in the fetuses. Clorazepate dipotassium did not alter the fertility indices or reproductive capacity of adult animals. As expected, the sedative effect of high doses interfered with care of the young by their mothers (see Usage in Pregnancy).

HOW SUPPLIED

Clorazepate dipotassium tablets, USP 7.5 mg are peach colored, round tablets, debossed with “ RX” above the break-line and “ 553” below the break-line on one side and plain on the other side. They are supplied as follows:

NDC 67046-904-07 blisterpacks of 7

NDC 67046-904-14 blisterpacks of 14

NDC 67046-904-15 blisterpacks of 15

NDC 67046-904-20 blisterpacks of 20

NDC 67046-904-21 blisterpacks of 21

NDC 67046-904-28 blisterpacks of 28

NDC 67046-904-30 blisterpacks of 30

NDC 67046-904-60 blisterpacks of 60

Clorazepate dipotassium tablets, USP 15 mg are red colored, round tablets debossed with “ RX” above the break-line and “ 554” below the break-line on one side and plain on the other side. They are supplied as follows:

NDC 67046-907-07 blisterpacks of 7

NDC 67046-907-14 blisterpacks of 14

NDC 67046-907-15 blisterpacks of 15

NDC 67046-907-20 blisterpacks of 20

NDC 67046-907-21 blisterpacks of 21

NDC 67046-907-28 blisterpacks of 28

NDC 67046-907-30 blisterpacks of 30

NDC 67046-907-60 blisterpacks of 60

Recommended storage: Protect from moisture. Keep bottle tightly closed.

Store at 20 - 25° C (68 - 77 ° F) [See USP Controlled Room Temperature].

Dispense in a USP tight, light–resistant container.

Manufactured for:

Ranbaxy Pharmaceuticals Inc.

Jacksonville, FL 32257 USA

by: Ohm Laboratories Inc.

North Brunswick, NJ 08902 USA

September 2010

MEDICATION GUIDE

CLORAZEPATE DIPOTASSIUM TABLETS, USP

Rx only

Read this Medication Guide before you start taking clorazepate dipotassium tablets, USP and each time you get a refill. There may be new information. This information does not take the place of talking to your healthcare provider about your medical condition or treatment.

What is the most important information I should know about clorazepate dipotassium tablets, USP?

Do not stop taking clorazepate dipotassium tablets, USP without first talking to your healthcare provider. Stopping clorazepate dipotassium tablets, USP suddenly can cause serious problems.

Clorazepate dipotassium tablets, USP can cause serious side effects, including:

1. Clorazepate dipotassium tablets, USP can make you sleepy or dizzy and can slow your thinking and motor skills

- Do not drive, operate heavy machinery, or do other dangerous activities until you know how clorazepate dipotassium tablets, USP affects you.
- Do not drink alcohol or take other drugs that may make you sleepy or dizzy while taking clorazepate dipotassium tablets, USP without first talking to your healthcare provider. When taken with alcohol or drugs that cause sleepiness or dizziness, clorazepate dipotassium tablets, USP may make your sleepiness or dizziness much worse.

2. Clorazepate dipotassium tablets, USP can cause abuse and dependence.

- Do not stop taking clorazepate dipotassium tablets, USP all of a sudden. Stopping clorazepate dipotassium tablets, USP suddenly can cause seizures that do not stop, hearing or seeing things that are not there (hallucinations), shaking, and stomach and muscle cramps.
  - Talk to your doctor about slowly stopping clorazepate dipotassium tablets, USP to avoid getting sick with withdrawal symptoms.
  - Physical dependence is not the same as drug addiction. Your healthcare provider can tell you more about the differences between physical dependence and drug addiction.

Clorazepate dipotassium tablets, USP is a federally controlled substance (C-IV) because it can be abused or lead to dependence. Keep clorazepate dipotassium tablets, USP in a safe place to prevent misuse and abuse. Selling or giving away clorazepate dipotassium tablets, USP may harm others, and is against the law. Tell your healthcare provider if you have ever abused or been dependent on alcohol, prescription medicines or street drugs.

3. Clorazepate dipotassium tablets, USP may harm your unborn or developing baby.

Medicines like clorazepate dipotassium tablets, USP can cause birth defects. Talk with your healthcare provider if you are pregnant or plan to become pregnant. Tell your healthcare provider right away if you become pregnant while taking clorazepate dipotassium tablets, USP. You and your healthcare provider should decide if you will take clorazepate dipotassium tablets, USP while you are pregnant. Birth defects may occur even in children born to women who are not taking any medicines and do not have other risk factors.

- If you become pregnant while taking clorazepate dipotassium tablets, USP, talk to your healthcare provider about registering with the North American Antiepileptic Drug Pregnancy Registry. You can register by calling 1-888-233-2334. The purpose of this registry is to collect information about the safety of antiepileptic drugs during pregnancy.
- Clorazepate dipotassium can pass into breast milk. Talk to your healthcare provider about the best way to feed your baby if you take clorazepate dipotassium tablets, USP. You and your healthcare provider should decide if you will take clorazepate dipotassium tablets, USP or breast feed. You should not do both.

4. Like other antiepileptic drugs, clorazepate dipotassium tablets, USP may cause suicidal thoughts or actions in a very small number of people, about 1 in 500.

Call your healthcare provider right away if you have any of these symptoms, especially if they are new, worse, or worry you:

- thoughts about suicide or dying
- attempts to commit suicide
- new or worse depression
- new or worse anxiety
- feeling agitated or restless
- panic attacks
- trouble sleeping (insomnia)
- new or worse irritability
- acting aggressive, being angry, or violent
- acting on dangerous impulses
- an extreme increase in activity and talking (mania)
- other unusual changes in behavior or mood

How can I watch for early symptoms of suicidal thoughts and actions?

- Pay attention to any changes, especially sudden changes, in mood, behaviors, thoughts, or feelings.
- Keep all follow-up visits with your healthcare provider as scheduled.

Call your healthcare provider between visits as needed, especially if you are worried about symptoms.

Do not stop clorazepate dipotassium tablets, USP without first talking to a healthcare provider.

Stopping clorazepate dipotassium tablets, USP suddenly can cause serious problems. Stopping a seizure medicine suddenly in a patient who has epilepsy can cause seizures that will not stop (status epilepticus).

Suicidal thoughts or actions can be caused by things other than medicines. If you have suicidal thoughts or actions, your healthcare provider may check for other causes.

What are clorazepate dipotassium tablets, USP?

Clorazepate dipotassium tablets, USP is a prescription medicine used:

- to treat anxiety disorders
- with other medicines to treat partial seizures
- to treat the symptoms of sudden alcohol withdrawal

Who should not take clorazepate dipotassium tablets, USP?

Do not take clorazepate dipotassium tablets, USP if you:

- are allergic to clorazepate dipotassium or any of the ingredients in clorazepate dipotassium tablets, USP. See the end of this Medication Guide for a complete list of ingredients in clorazepate dipotassium tablets, USP.
- have an eye disease called acute narrow angle glaucoma.

What should I tell my healthcare provider before taking clorazepate dipotassium tablets, USP?

Before you take clorazepate dipotassium tablets, USP, tell your healthcare provider if you:

- have liver or kidney problems
- have or have had depression, mood problems, or suicidal thoughts or behavior
- have a history of abnormal thinking and behavior (psychotic reactions)
- have any other medical conditions

Tell your healthcare provider about all the medicines you take, including prescription and nonprescription medicines, vitamins, and herbal supplements. Taking clorazepate dipotassium tablets, USP with certain other medicines can cause side effects or affect how well they work. Do not start or stop other medicines without talking to your healthcare provider.

Know the medicines you take. Keep a list of them and show it to your healthcare provider and pharmacist when you get a new medicine.

How should I take clorazepate dipotassium tablets, USP?

- Take clorazepate dipotassium tablets, USP exactly as prescribed. Your healthcare provider will tell you how much clorazepate dipotassium tablets, USP to take.
- Your healthcare provider may change your dose. Do not change your dose of clorazepate dipotassium tablets, USP without talking to your healthcare provider.
- Do not stop taking clorazepate dipotassium tablets, USP without first talking to your healthcare provider. Stopping clorazepate dipotassium tablets, USP suddenly can cause serious problems.

If you take too much clorazepate dipotassium tablets, USP, call your healthcare provider or local Poison Control Center right away.

What are the possible side effects of clorazepate dipotassium tablets, USP? See “What is the most important information I should know about clorazepate dipotassium tablets, USP?”.

The most common side effects of clorazepate dipotassium tablets, USP include:

- drowsiness
- dizziness
- upset stomach
- blurred vision
- dry mouth
- confusion

These are not all the possible side effects of clorazepate dipotassium tablets, USP. For more information ask your healthcare provider or pharmacist.

Tell your healthcare provider if you have any side effect that bothers you or that does not go away.

Call your doctor for medical advice about side effects. You may report side effects to FDA at 1-800-FDA-1088.

How should I store clorazepate dipotassium tablets, USP?

- Store clorazepate dipotassium tablets, USP between 68○F to 77○F (20○C to 25○C).
- Keep clorazepate dipotassium tablets, USP in a tightly closed container.
- Keep clorazepate dipotassium tablets, USP out of the light.
- Keep clorazepate dipotassium tablets, USP dry.

Keep clorazepate dipotassium tablets, USP and all medicines away from children.

General Information about clorazepate dipotassium tablets, USP

Medicines are sometimes prescribed for purposes other than those listed in a Medication Guide. Do not use clorazepate dipotassium tablets, USP for a condition for which it was not prescribed. Do not give clorazepate dipotassium tablets, USP to other people, even if they have the same symptoms that you have. It may harm them.

This Medication Guide summarizes the most important information about clorazepate dipotassium tablets, USP. If you would like more information, talk with your healthcare provider. You can ask your pharmacist or healthcare provider for information about clorazepate dipotassium tablets, USP that is written for health professionals.

For more information about clorazepate dipotassium tablets, USP, go to www.ranbaxyusa.com or call Ranbaxy Pharmaceuticals Inc. at 1-888-Ranbaxy (726-2299).

What are the ingredients in clorazepate dipotassium tablets, USP?

Active ingredient: clorazepate dipotassium, USP

Inactive ingredients: colloidal silicon dioxide, magnesium oxide, magnesium stearate, microcrystalline cellulose, potassium carbonate, and potassium chloride.

In addition:

- the 3.75 mg tablets contain FD&C Blue No. 2 aluminum lake
- the 7.5 mg tablets contain FD&C Yellow No. 6 aluminum lake
- the 15 mg tablets contain FD&C Red No. 40 aluminum lake

This Medication Guide has been approved by the U.S. Food and Drug Administration.

Manufactured for:

Ranbaxy Pharmaceuticals Inc.

Jacksonville, FL 32257 USA

by: Ohm Laboratories Inc.

North Brunswick, NJ 08902 USA

September 2010

Repackaged by:
Contract Pharmacy Services-PA
125 Titus Ave Suite 200
Warrington, PA 18976 USA

Rev: Original—2017.09.28—NJW

PACKAGE LABEL. PRINCIPAL DISPLAY PANEL

Clorazepate dipotassium tablets, USP, 7.5 mg

RANBAXY

NDC 67046-904-30

Clorazepate dipotassium tablets, USP, 7.5 mg

PHARMACIST: Dispense the accompanying Medication Guide to each patient*

Rx only 30 Tablets

Clorazepate dipotassium tablets, USP, 15 mg

RANBAXY

NDC 67046-907-30

Clorazepate dipotassium tablets, USP, 15 mg

PHARMACIST: Dispense the accompanying Medication Guide to each patient*

Rx only 30 Tablets